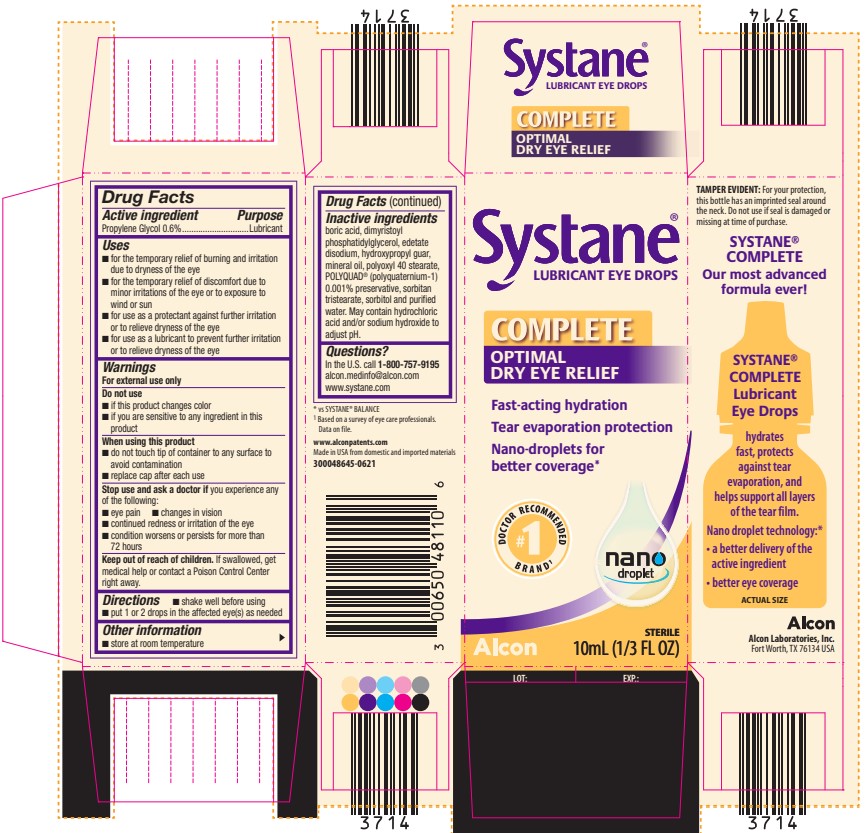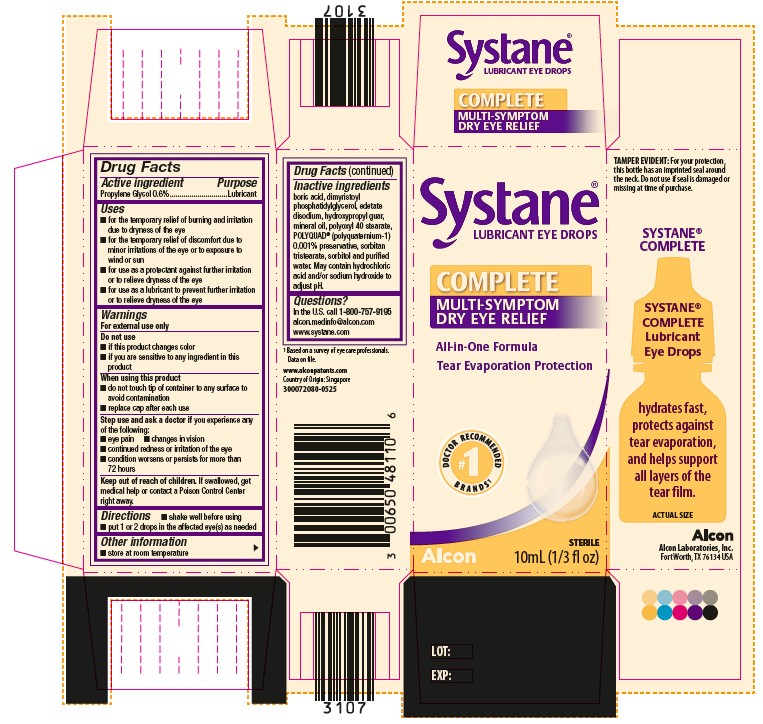 DRUG LABEL: Systane COMPLETE
NDC: 0065-0481 | Form: EMULSION
Manufacturer: Alcon Laboratories, Inc.
Category: otc | Type: HUMAN OTC DRUG LABEL
Date: 20250808

ACTIVE INGREDIENTS: Propylene Glycol .06 mg/1 mL
INACTIVE INGREDIENTS: Boric Acid; Dimyristoylphosphatidylglycerol, Dl-; Edetate Disodium; Guar Gum; Mineral Oil; Polyoxyl 40 Stearate; Sorbitan Tristearate; Sorbitol; Water; Hydrochloric Acid; Sodium Hydroxide; Polidronium Chloride

Systane COMPLETE Lubricant Eye Drops
Drug Facts

Active Ingredients | Purpose
Propylene Glycol 0.6% | Lubricant

Uses

- for the temporary relief of burning and irritation due to dryness of the eye
- for the temporary relief of discomfort due to minor irritations of the eye or to exposure to wind or sun
- for use as a protectant against further irritation or to relieve dryness of the eye
- for use as a lubricant to prevent further irritation or to relieve dryness of the eye

Warnings

For external use only

Do not use

- if this product changes color
- if you are sensitive to any ingredient in this product

When using this product

- do not touch tip of container to any surface to avoid contamination
- replace cap after each use

Stop use and ask a doctor if you experience any of the following:

- eye pain
- changes in vision
- continued redness or irritation of the eye
- condition worsens or persists for more than 72 hours

Keep out of reach of children.
If swallowed, get medical help or contact a Poison Control Center right away.

Directions

- shake well before using
- put 1 or 2 drops in the affected eye(s) as needed

Other Information

- store at room temperature

Inactive Ingredients

boric acid, dimyristoyl phosphatidylglycerol, edetate disodium, hydroxypropyl guar, mineral oil, polyoxyl 40 stearate, POLYQUAD® (polyquaternium-1) 0.001% preservative, sorbitan tristearate, sorbitol and purified water. May contain hydrochloric acid and/or sodium hydroxide to adjust pH.

Questions?

In the U.S. call 1-800-757-9195
alcon.medinfo@alcon.com
www.systane.com

PRINCIPAL DISPLAY PANEL

Systane®
LUBRICANT EYE DROPS
COMPLETE
OPTIMAL DRY EYE RELIEF
Fast-acting hydration
Tear evaporation protection
Nano-droplets for better coverage*
#1 DOCTOR RECOMMENDED BRAND^1
nano droplet
Alcon
STERILE
10mL (1/3 FL OZ)
LOT: EXP.:

SIDE PANEL
TAMPER EVIDENT: For your protection,
this bottle has an imprinted seal around
the neck. Do not use if seal is damaged or
missing at time of purchase.
SYSTANE®
COMPLETE
Our most advanced
formula ever!
SYSTANE®
COMPLETE
Lubricant
Eye Drops
hydrates
fast, protects
against tear
evaporation, and
helps support all layers
of the tear film.
Nano droplet technology:*
● a better delivery of the
active ingredient
● better eye coverage
ACTUAL SIZE
Alcon
Alcon Laboratories, Inc.
Fort Worth, TX 76143 USA
* vs SYSTANE® BALANCE
^1Based on a survey of eye care professionals.
Data on file.
www.alconpatents.com
Made in USA from domestic and imported materials
300048645-0621

Systane®
LUBRICANT EYE DROPS
COMPLETE
MULTI-SYMPTOM
DRY EYE RELIEF
All-in-One Formula
Tear Evaporation Protection
#1 DOCTOR RECOMMENDED BRANDS^1
Alcon
STERILE
10mL (1/3 fl oz)
LOT: EXP.:
SIDE PANEL
TAMPER EVIDENT: For your protection,
this bottle has an imprinted seal around
the neck. Do not use if seal is damaged or
missing at time of purchase.
SYSTANE®
COMPLETE
SYSTANE®
COMPLETE
Lubricant
Eye Drops
hydrates
fast, protects
against tear
evaporation, and
helps support all layers
of the tear film.
ACTUAL SIZE
Alcon
Alcon Laboratories, Inc.
Fort Worth, TX 76143 USA
^1Based on a survey of eye care professionals.
Data on file.
www.alconpatents.com
Country of Origin: Singapore
300072080-0525